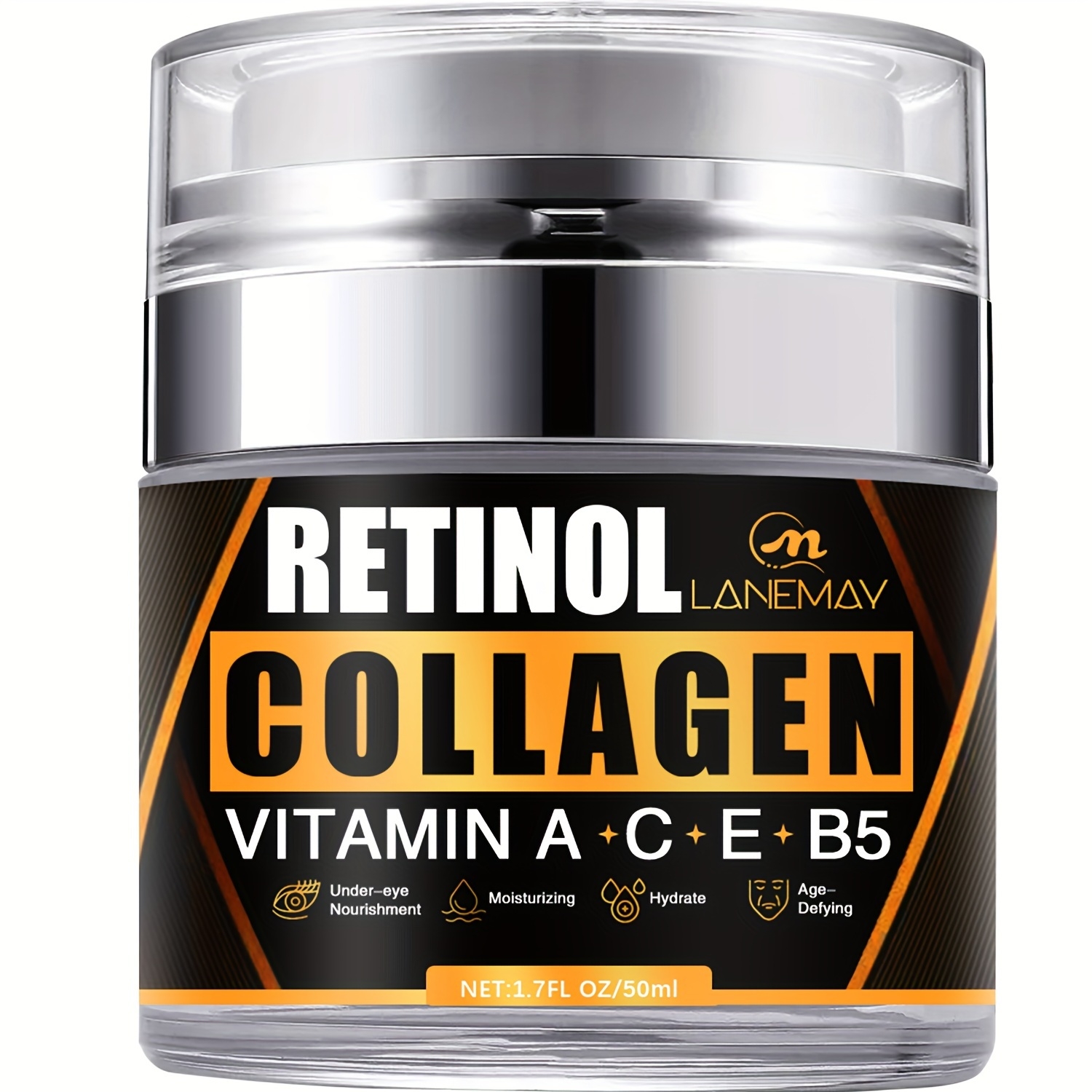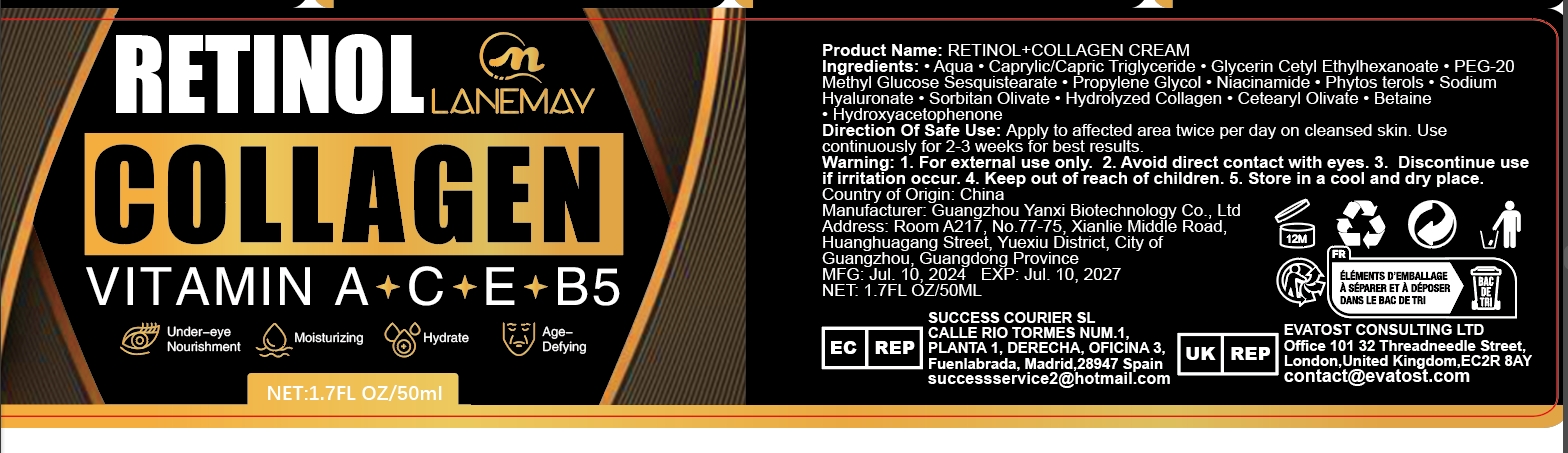 DRUG LABEL: Retinol Collagen Cream
NDC: 84025-187 | Form: CREAM
Manufacturer: Guangzhou Yanxi Biotechnology Co.. Ltd
Category: otc | Type: HUMAN OTC DRUG LABEL
Date: 20240912

ACTIVE INGREDIENTS: PEG-20 METHYL GLUCOSE SESQUISTEARATE 3 mg/50 mL; CAPRYLIC/CAPRIC/LAURIC TRIGLYCERIDE 5 mg/50 mL
INACTIVE INGREDIENTS: WATER

DOSAGE AND ADMINISTRATION

Cream for moisturizing the skin and reducing fine lines

WARNINGS

keep out of children

INACTIVE INGREDIENT

AQUA

INDICATIONS AND USAGE

For daily facial skin care

keep out of children

PURPOSE

Effectively nourishes the skin and resists skin aging